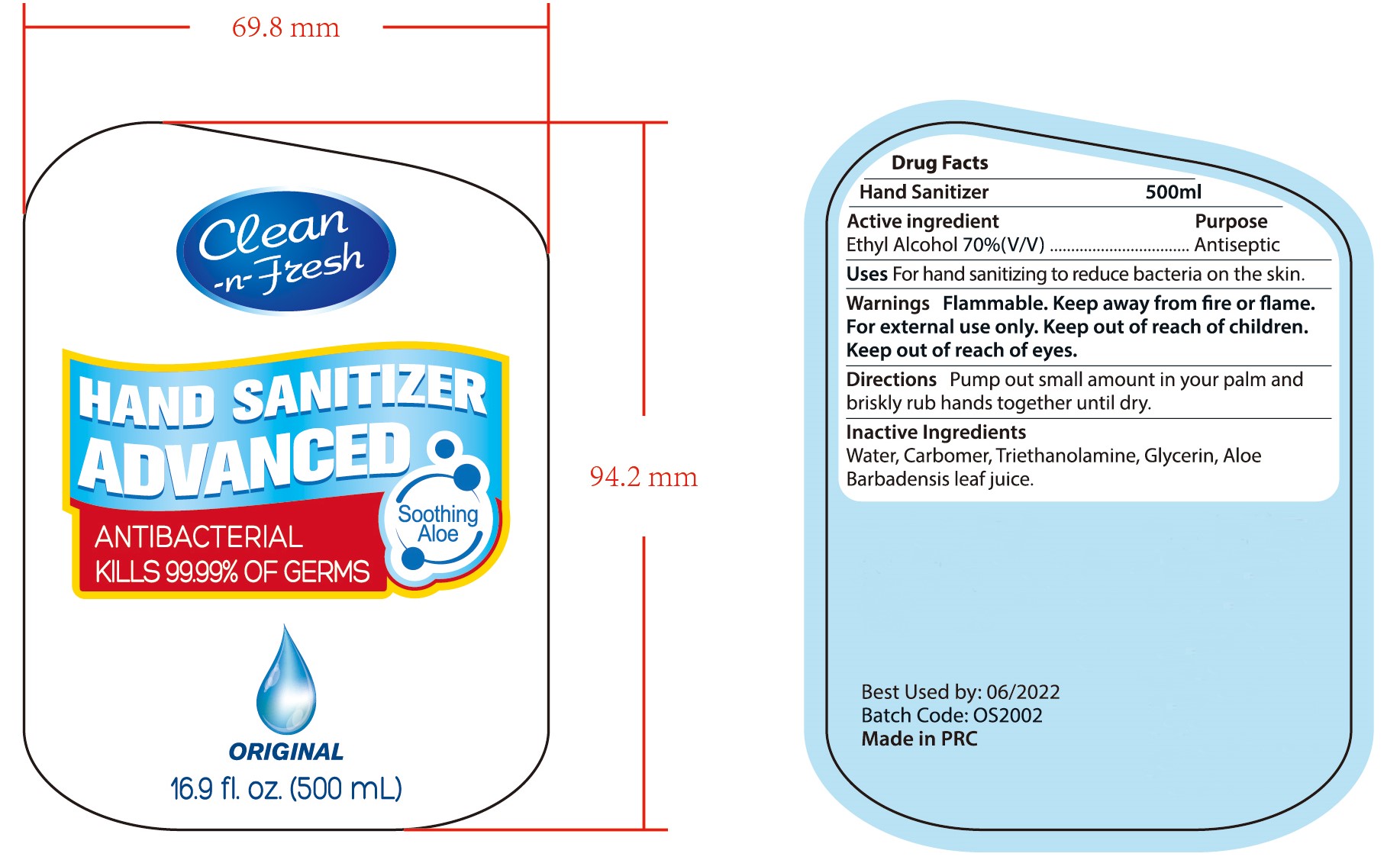 DRUG LABEL: HAND SANITIZER
NDC: 47993-281 | Form: GEL
Manufacturer: NINGBO JIANGBEI OCEAN STAR TRADING CO.,LTD
Category: otc | Type: HUMAN OTC DRUG LABEL
Date: 20201105

ACTIVE INGREDIENTS: ALCOHOL 70 mL/100 mL
INACTIVE INGREDIENTS: CARBOMER 940; TRIETHANOLAMINE BENZOATE; ALOE VERA LEAF; WATER; GLYCERIN

47993-281

Active ingredients

Ethyl Alcohol 70%(V/V)

PURPOSE

Antiseptic

Uses：

For hand sanitizing to reduce bacteria on the skin.

Warnings:

Flammable. Keep away from fire or flame. For external use only.

Keep out of reach of children.

WHEN USING

Keep out of reach of eyes.

Directions:

Pump out small amount in your palm and briskly rub hands together until dry.

Inactive Ingredients:

Water,Carbomer,Triethanolamine,Glycerin,Aloe Barbadensis leaf juice